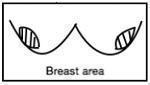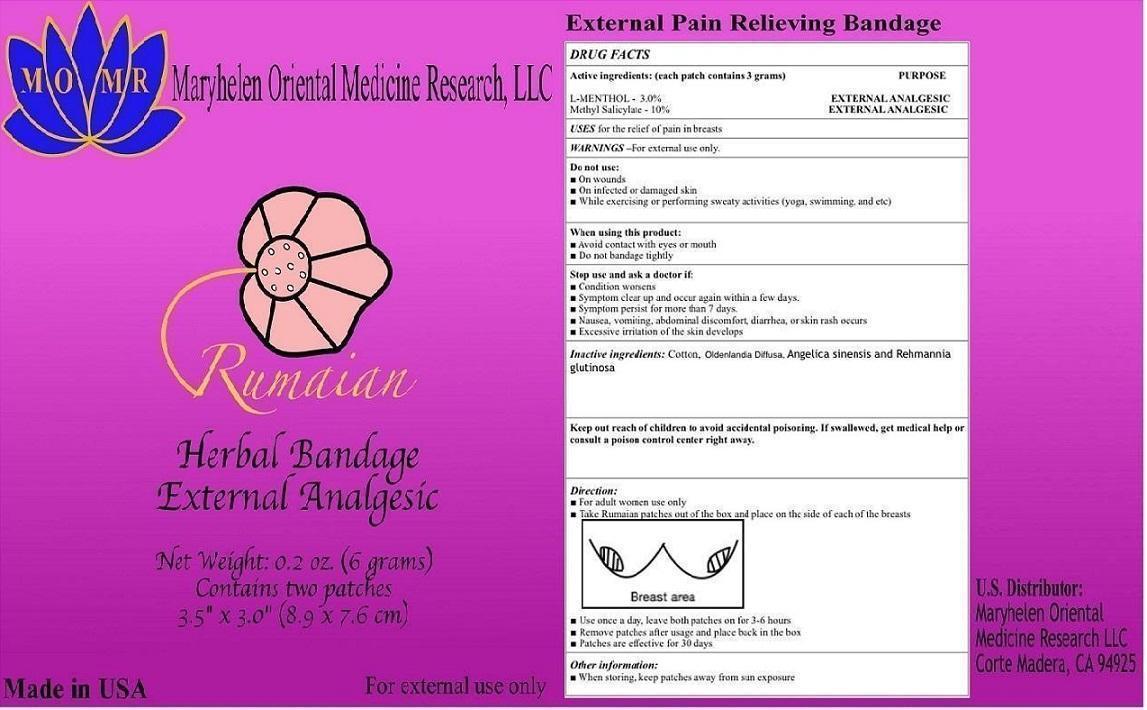 DRUG LABEL: MOMR Rumaian Herbal Bandage
NDC: 69559-3921 | Form: PATCH
Manufacturer: MARYHELEN ORIENTAL MEDICINE RESEARCH
Category: otc | Type: HUMAN OTC DRUG LABEL
Date: 20150201

ACTIVE INGREDIENTS: LEVOMENTHOL 0.09 g/1 1; METHYL SALICYLATE 0.3 g/1 1
INACTIVE INGREDIENTS: COTTON FIBER; OLDENLANDIA DIFFUSA; ANGELICA SINENSIS WHOLE; REHMANNIA GLUTINOSA WHOLE

MOMR Rumaian Herbal Bandage

Active ingredients: (each patch contains 3 grams)

L-MENTHOL – 3.0%
Methyl Salicylate – 10%

PURPOSE

EXTERNAL ANALGESIC

KEEP OUT OF REACH OF CHILDREN

Keep out reach of children to avoid accidental poisoning. If swallowed, get medical help or consult a poison control center right away.

INDICATIONS AND USAGE

USES for the relief of pain in breasts.

WARNINGS – For external use only.

Do not use:
• On wounds
• On infected or damaged skin
• While exercising or performing sweaty activities (yoga, swimming, and etc.,)

When using this product:
• Avoid contact with eyes or mouth
• Do not bandage tightly

Stop use and ask a doctor if:
• Condition worsens
• Symptom clear up and occur again within a few days.
• Symptom persist for more than 7 days.
• Nausea, vomiting, abdominal discomfort, diarrhea, or skin rash occurs.
• Excessive irritation of the skin develops

Direction:

• For adult women use only
• Take Rumaian patches out of the box and place on the side of each of the breasts.

• Use once a day, leave both patches on for 3-6 hours
• Remove patches after usage and place back in the box
• Patches are effective for 30 days

Other information:

• When storing, keep patches away from sun exposure

INACTIVE INGREDIENT

Inactive ingredients: Cotton, Oldenlandia Diffusa, Angelica sinensis and Rehmannia glutinosa.